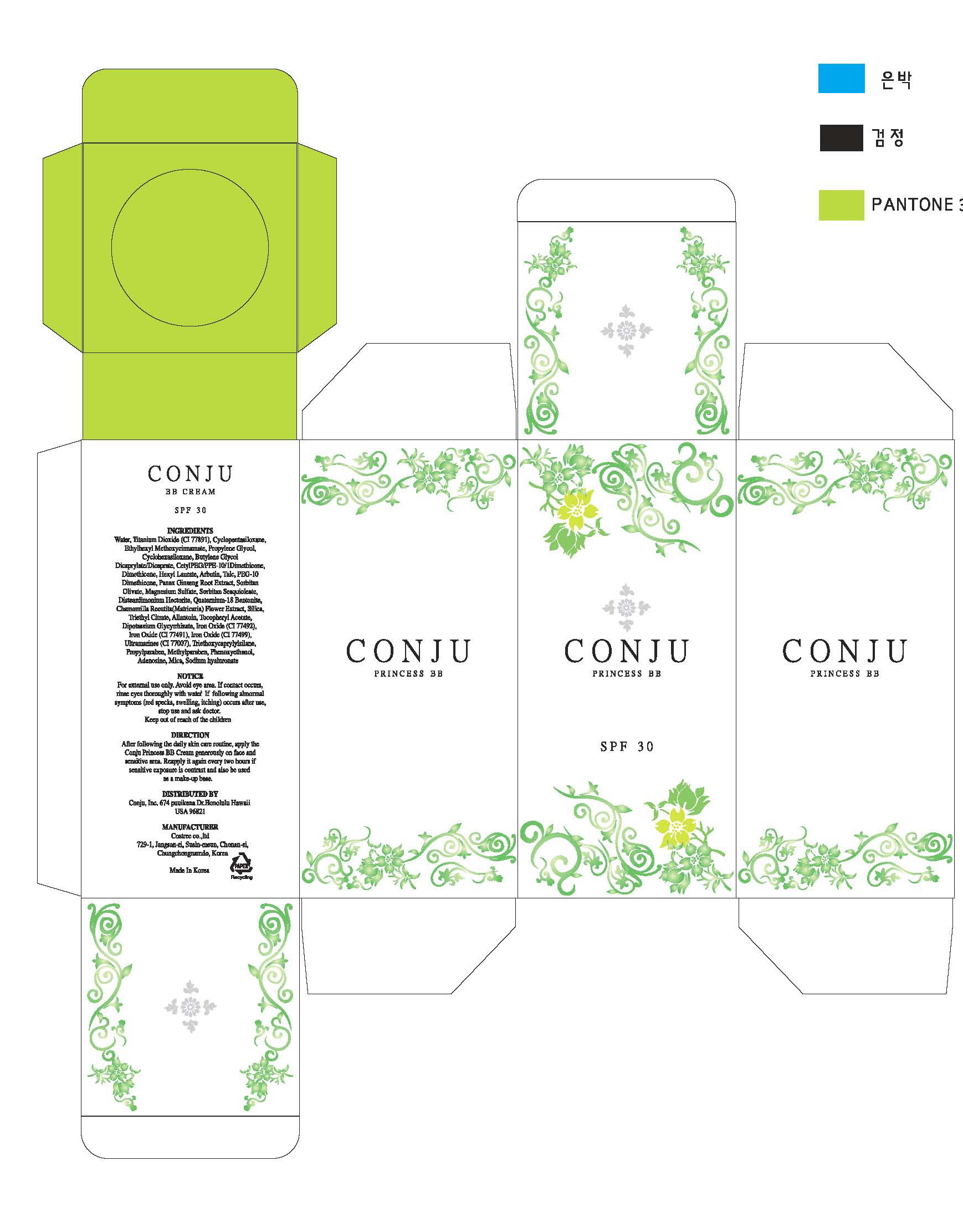 DRUG LABEL: Conju Princess BB
NDC: 59915-1001 | Form: CREAM
Manufacturer: Conju Inc
Category: otc | Type: HUMAN OTC DRUG LABEL
Date: 20110124

ACTIVE INGREDIENTS: TITANIUM DIOXIDE 10.15 mL/100 mL; ARBUTIN 2 mL/100 mL; ADENOSINE 0.04 mL/100 mL
INACTIVE INGREDIENTS: WATER; CYCLOMETHICONE 5; OCTINOXATE; PROPYLENE GLYCOL; CYCLOMETHICONE 6; BUTYLENE GLYCOL; DIMETHICONE; HEXYL LAURATE; TALC; ASIAN GINSENG; SORBITAN OLIVATE; MAGNESIUM SULFATE, UNSPECIFIED; SORBITAN SESQUIOLEATE; HECTORITE; BENTONITE; CHAMOMILE; SILICON DIOXIDE; TRIETHYL CITRATE; ALLANTOIN; .ALPHA.-TOCOPHEROL ACETATE, DL-; LICORICE; FERRIC OXIDE RED; FERRIC OXIDE YELLOW; FERROSOFERRIC OXIDE; OCTYLTRIETHOXYSILANE; PROPYLPARABEN; METHYLPARABEN; PHENOXYETHANOL; MICA; HYALURONATE SODIUM

Drug Facts

Active ingredient: titanium dioxide, arbutin, adenosine

Inactive ingredient: water, titanium dioxide,cyclopentasiloxzne, ethylhexyl methoxycinnamate,propylene glycol, cyclohexasiloxane, butylene glycol dicaprylate/dicaprate, cetyl/peg/ppe-10/1 dimethicone, dimethicone,hexyl laurate, arbutin, tale, PEG-10 dimethicone, panax ginseng root extract, sorbitan, olivate, magnesium sulfate, sorbitan sesquioleate, disteardimonium hectorite,quaternium-19bentonite, chamomilla recutita (matricaria) flower extract, silica, triethyl citrate, allantoin, tocopheryl acetate, dipotassium clycyrrhizate, iron oxide (CI 77492), iron oxide (CI 77491), iron oxide (CI 77499), ultramarines (CI 77007), triethoxycaprylylsilane, propylparaben, methylparaben, phenoxyethanol, adenosine, mica, sodim hyaluronate

PURPOSE

helps prevent sunburn

keep out of reach of the children

INDICATIONS AND USAGE

After following the daily skin care routine, apply the Conju Princess BB Cream generously onface and sensitive area. Reapply it again every two hours if sensitive exposure is contrast and also be used as a make-up base

Warning
For external use only
When using this product
■ Avoid eye area. If contact occurs, rinse eyes thoroughly　with water
■ If following abnormal symptoms occurs after use, stop use and ask doctor
red specks, swelling, itching

DOSAGE AND ADMINISTRATION

- for external use only
- apply frequently when needed